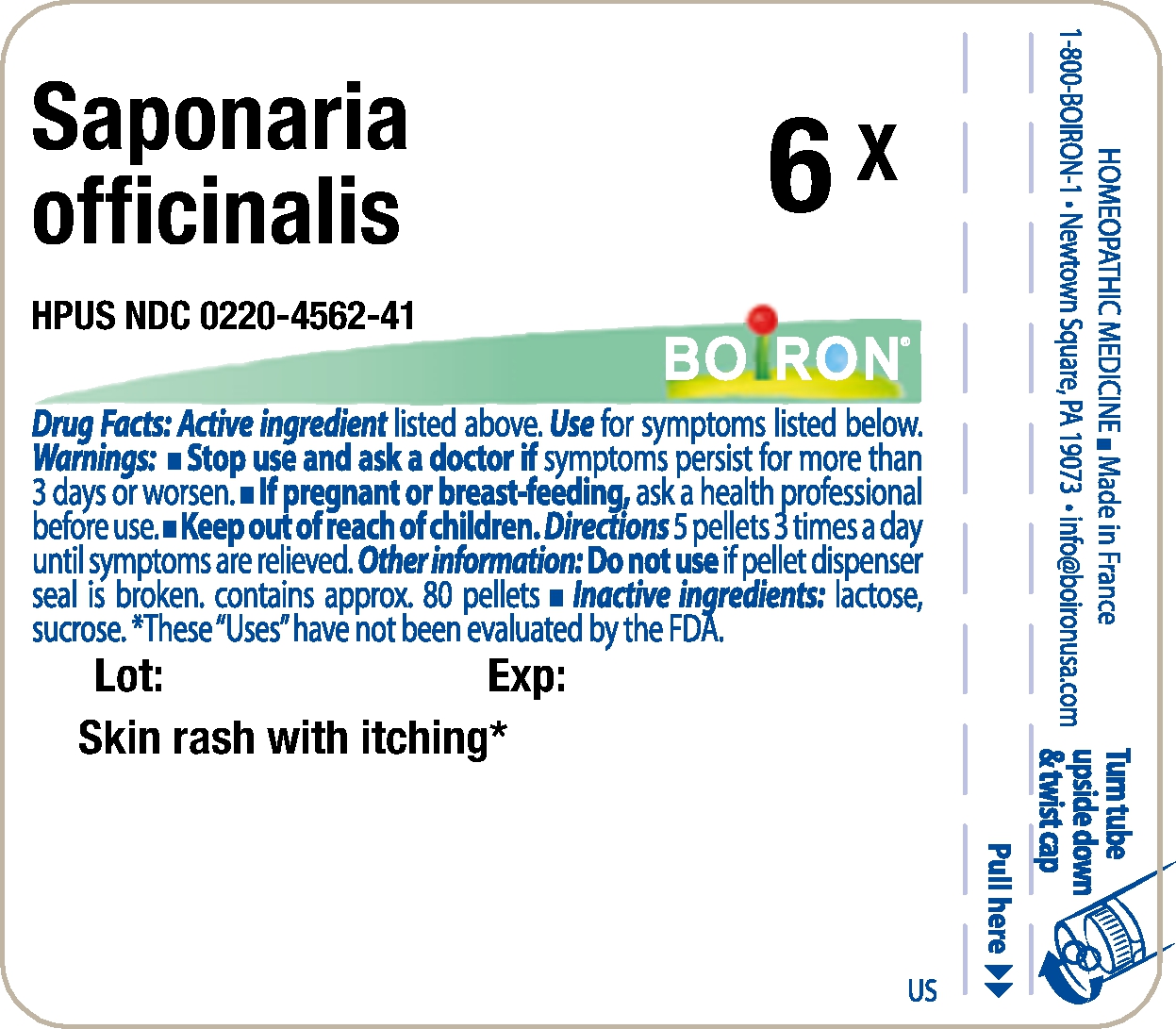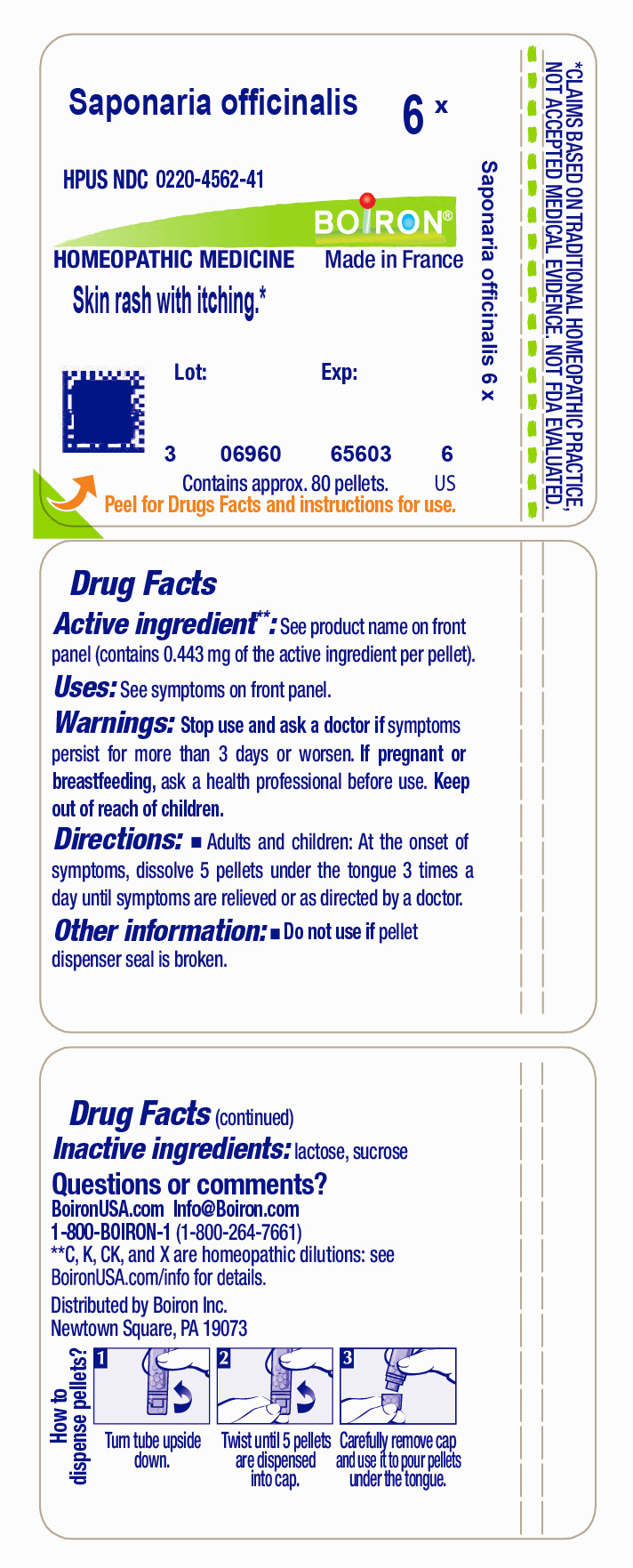 DRUG LABEL: Saponaria officinalis
NDC: 0220-4562 | Form: PELLET
Manufacturer: Laboratoires Boiron
Category: homeopathic | Type: HUMAN OTC DRUG LABEL
Date: 20231114

ACTIVE INGREDIENTS: SAPONARIA OFFICINALIS ROOT 6 [hp_X]/1 1
INACTIVE INGREDIENTS: SUCROSE; LACTOSE

Saponaria officinalis 6X

Active Ingredients

Saponaria officinalis 6X

(**contains 0.443 mg of the active ingredient per pellet)

Use

Skin rash with itching*

Warnings

Stop use and ask a doctor if

symptoms persist for more than 3 days or worsen.

If pregnant or breast-feeding,

ask a health professional before use.

Directions

Adults and children: At the onset of symptoms, dissolve 5 pellets under the tongue 3 times a day until symptoms are relieved or as directed by a doctor.

Other information

Do not use if pellet dispenser seal is broken.
contains approx. 80 pellets

Inactive ingredients

lactose, sucrose

Questions, Comments?

1-800-BOIRON-1
Newtown Square, PA 19073-3267
info@boironusa.com

*

Do not use if pellet dispenser seal is broken.
Contains approx 80 pellets.
How to dispense pellets? Turn tube upside down. Twist until 5 pellets are dispensed into cap. Carefully remove the cap and use it to pour pellets under the tongue.
*CLAIMS BASED ON TRADITIONAL HOMEOPATHIC PRACTICE NOT ACCEPTED MEDICAL EVIDENCE. NOT FDA EVALUATED.
**C,K,CK, and X are homeopathic dilutions: see BoironUSA.com/info for details.